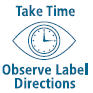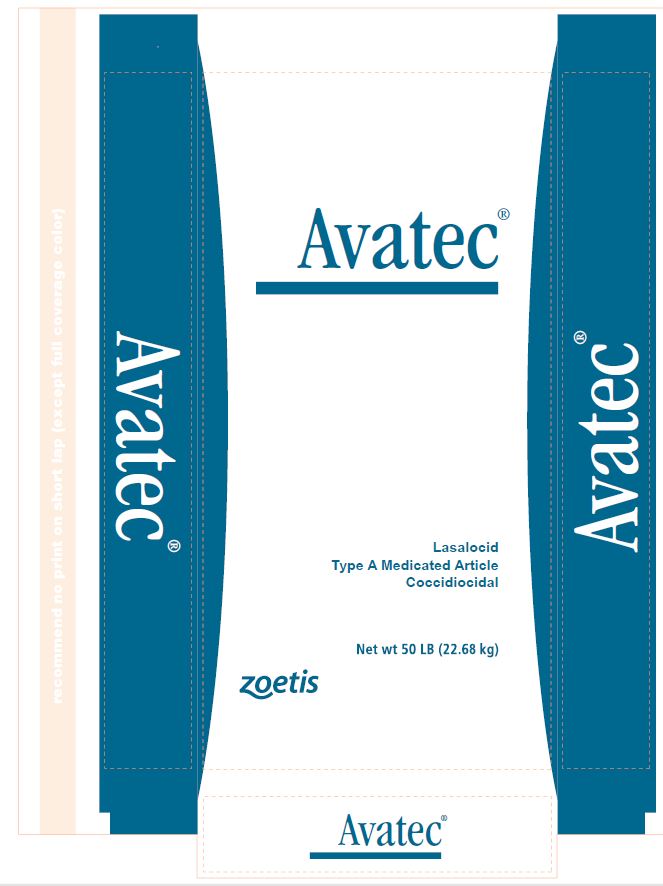 DRUG LABEL: Avatec
NDC: 54771-1313 | Form: GRANULE
Manufacturer: Zoetis Inc.
Category: animal | Type: OTC TYPE A MEDICATED ARTICLE ANIMAL DRUG LABEL
Date: 20200610

ACTIVE INGREDIENTS: LASALOCID SODIUM 90.7 g/0.45 kg

Avatec®

Avatec®

Lasalocid
Type A Medicated Article
Coccidiocidal

Active drug ingredient

Each pound contains 90.7 grams (20%) of lasalocid (as lasalocid sodium activity) in a carrier suitable for incorporation in feed.

For use in the manufacture of medicated feeds only

INDICATIONS AND USAGE

For the prevention of coccidiosis in

Target Species: | Caused by:
Broiler or Fryer Chickens: | Eimeria tenella, E. necatrix, E. acervulina, E. brunetti, E. mivati, and E. maxima
Growing Turkeys: | E. meleagrimitis, E. gallopavonis, E. adenoeides
Rabbits: | Eimeria stiedae
Chukar Partridges: | Eimeria legionensis

Directions for use

Broiler, Fryer Chickens and Growing Turkeys
Use Avatec® continuously in the feed to provide from 68 g per ton (0.0075%) to 113 g per ton (0.0125%) lasalocid concentration. The dosage range allows adjustment of drug level to severity of exposure. The higher levels are indicated for severe exposure. Consult a poultry disease diagnostician for advice regarding the optimal level of drug.
Rabbits
Use Avatec® continuously in the feed for rabbits up to 6 1/2 weeks of age to provide 113 g per ton (0.0125%) lasalocid concentration.
Chukar Partridges
Use Avatec® continuously in the feed for young birds up to 8 weeks of age to provide 113 g per ton (0.0125%) lasalocid concentration.

Mixing directions

Thoroughly mix the following amounts of Avatec® to make one ton of feed to provide from 68 g per ton (0.0075%) to 113 g per ton (0.0125%) lasalocid concentration. When adding less than one pound of Type A medicated article per ton of feed, it is recommended that the Type A medicated article first be mixed with a small amount of feed (10-25 lbs.) prior to incorporation into the final feed.

Dosage for use in target species | Concentration % in Feed | Lasalocid grams/ton | lbs Avatec® per ton feed
Broiler, Fryer Chickens and Growing Turkeys | 0.0075% 0.0100% 0.01125% | 68 90.7 102 | 3/4 1 1 1/8
Broiler, Fryer Chickens, Growing Turkeys, Rabbits, Chukar Partridges | 0.0125% | 113 | 1 1/4

Warning

When mixing and handling lasalocid Type A medicated article, use protective clothing, impervious gloves and a dust mask. Avoid contact with eyes. Operators should wash thoroughly with soap and water after handling.

Withdrawal Periods

No withdrawal period is required when used according to labeling.

Note: In addition to label statements of identity, ingredients and directions for use, labeling of feeds containing Avatec® must contain the following statements:

FOR BROILER OR FRYER CHICKENS ONLY and/or
FOR GROWING TURKEYS ONLY and/or
FOR CHUKAR PARTRIDGES (UP TO EIGHT WEEKS OF AGE) ONLY and/or
FOR RABBITS (UP TO SIX AND ONE HALF WEEKS OF AGE) ONLY
Restricted drug (California) - Use only as directed.
Not for human use.
Additionally, all feed labeling must state:
FEED CONTINUOUSLY AS THE SOLE RATION

Store below 25°C (77°F), excursions permitted to 37°C (99°F).
Approved by FDA under NADA # 096-298
zoetis
Distributed by:
Zoetis Inc.
Kalamazoo, MI 49007

Net wt 50 LB (22.68 kg)

40030542

PRINCIPAL DISPLAY PANEL - 50 LB Label

Avatec®

Lasalocid
Type A Medicated Article
Coccidiocidal

Net wt 50 LB (22.68 kg)

Zoetis

Avatec Bag Label